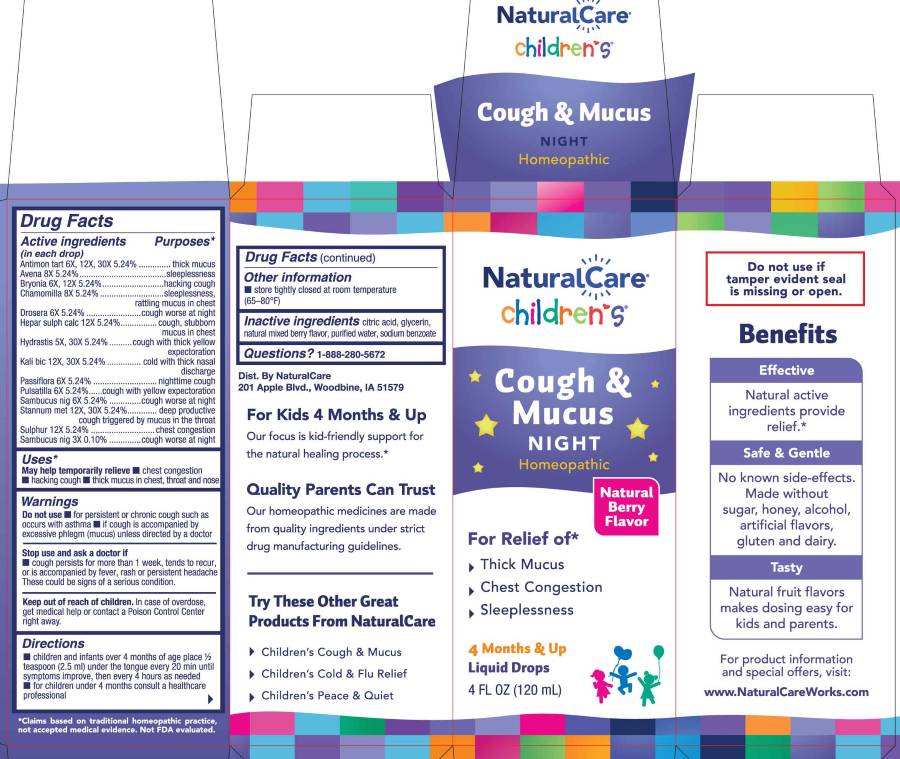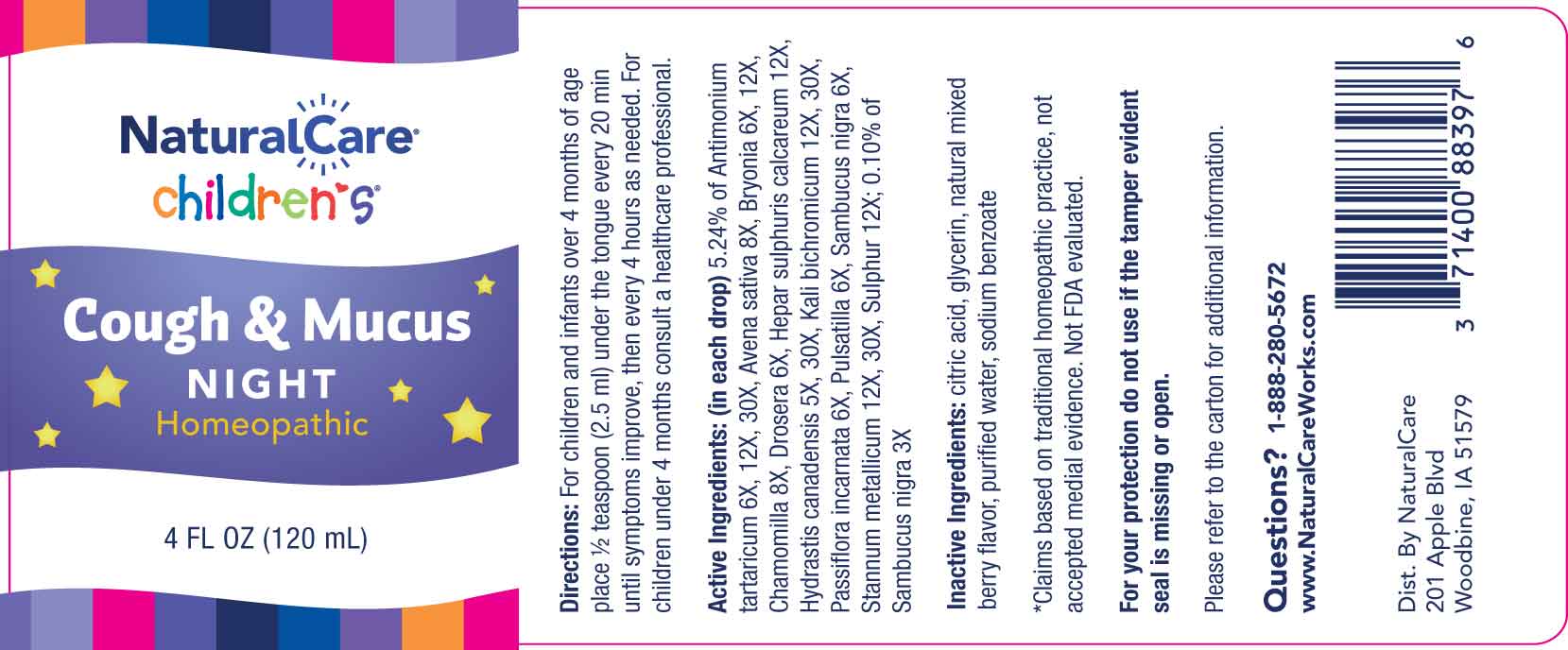 DRUG LABEL: Cough and Mucus Night
NDC: 70163-0024 | Form: LIQUID
Manufacturer: NaturalCare
Category: homeopathic | Type: HUMAN OTC DRUG LABEL
Date: 20260202

ACTIVE INGREDIENTS: ANTIMONY POTASSIUM TARTRATE 6 [hp_X]/1 mL; AVENA SATIVA FLOWERING TOP 8 [hp_X]/1 mL; BRYONIA ALBA ROOT 6 [hp_X]/1 mL; MATRICARIA CHAMOMILLA WHOLE 8 [hp_X]/1 mL; DROSERA ROTUNDIFOLIA WHOLE 6 [hp_X]/1 mL; CALCIUM SULFIDE 12 [hp_X]/1 mL; GOLDENSEAL 5 [hp_X]/1 mL; POTASSIUM DICHROMATE 12 [hp_X]/1 mL; PASSIFLORA INCARNATA FLOWERING TOP 6 [hp_X]/1 mL; PULSATILLA PRATENSIS WHOLE 6 [hp_X]/1 mL; SAMBUCUS NIGRA FLOWERING TOP 3 [hp_X]/1 mL; TIN 12 [hp_X]/1 mL; SULFUR 12 [hp_X]/1 mL
INACTIVE INGREDIENTS: CITRIC ACID MONOHYDRATE; GLYCERIN; WATER; SODIUM BENZOATE

DRUG FACTS:

ACTIVE INGREDIENT:

(in each drop) 5.24% of Antimonium Tartaricum 6X, 12X, 30X, Avena Sativa 8X, Bryonia 6X, 12X, Chamomilla 8X, Drosera 6X, Hepar Sulphuris Calcareum 12X, Hydrastis Canadensis 5X, 30X, Kali Bichromicum 12X, 30X, Passiflora Incarnata 6X, Pulsatilla 6X, Sambucus Nigra 6X, Stannum Metallicum 12X, 30X, Sulphur 12X; 0.10% of Sambucus Nigra 3X.

PURPOSE:

Antimonium Tartaricum – thick mucus, Avena Sativa - sleeplessness, Bryonia – hacking cough, Chamomilla – sleeplessness, rattling mucus in chest, Drosera – cough worse at night, Hepar Sulphuris Calcareum – cough, stubborn mucus in chest, Hydrastis Canadensis – cough with thick yellow expectoration, Kali Bichromicum – cold with thick nasal discharge, Passiflora Incarnata – nighttime cough, Pulsatilla – cough with yellow expectoration, Sambucus Nigra – cough worse at night, Stannum Metallicum – deep productive cough triggered by mucus in the throat, Sulphur – chest congestion*

*Claims based on traditional homeopathic practice, not accepted medical evidence. Not FDA evaluated.

USES:

May help temporarily relieve ■ chest congestion ■ hacking cough ■ thick mucus in chest, throat and nose*

*Claims based on traditional homeopathic practice, not accepted medical evidence. Not FDA evaluated.

WARNINGS:

Do not use

■ for persistent or chronic cough such as occurs with asthma ■ if cough is accompanied by excessive phlegm (mucus) unless directed by a doctor.

Stop use and ask a doctor if

■ cough persists for more than 1 week, tends to recur, or is accompanied by fever, rash or persistent headache.

These could be signs of a serious condition

Keep out of reach of children. In case of overdose, get medical help or contact a Poison Control Center right away.

Do not use if tamper evident seal is missing or open.

■ Store tightly closed at room temperature (65-80ºF)

KEEP OUT OF REACH OF CHILDREN:

In case of overdose, get medical help or contact a Poison Control Center right away.

DIRECTIONS:

■ children and infants over 4 months of age place 1/2 teaspoon (2.5 ml) under the tongue every 20 min until symptoms improve, then every 4 hours as needed.

■ for children under 4 months consult a healthcare professional.

INACTIVE INGREDIENTS:

citric acid, glycerin, natural mixed berry flavor, purified water, sodium benzoate

QUESTIONS:

Dist. By NaturalCare

201 Apple Blvd.

Woodbine, IA 51579

www.NaturalCareWorks.com

1-888-280-5672

PACKAGE LABEL DISPLAY:

NaturalCare

children's

Cough & Mucus

Night

Homeopathic

4 FL OZ (120 mL)